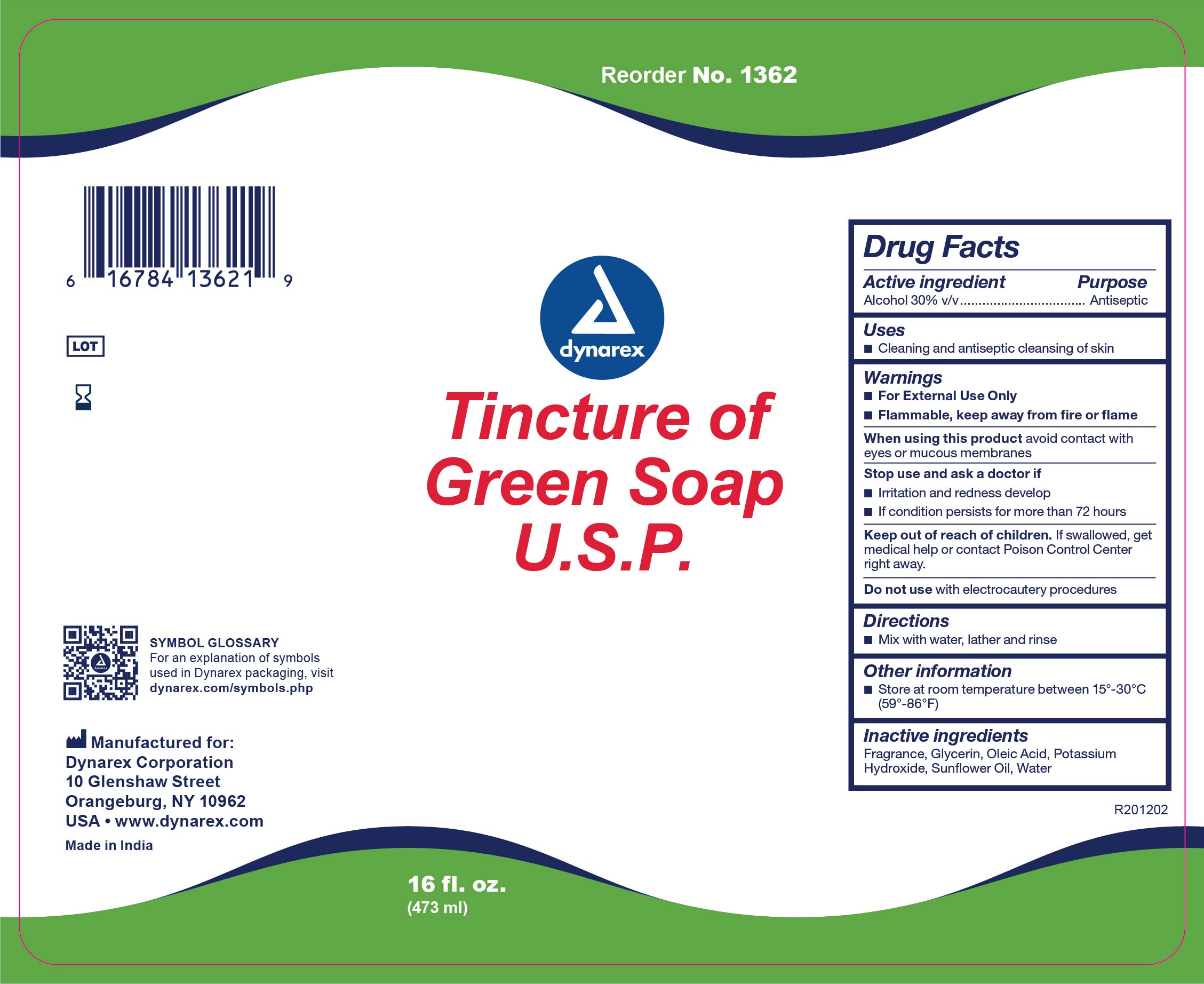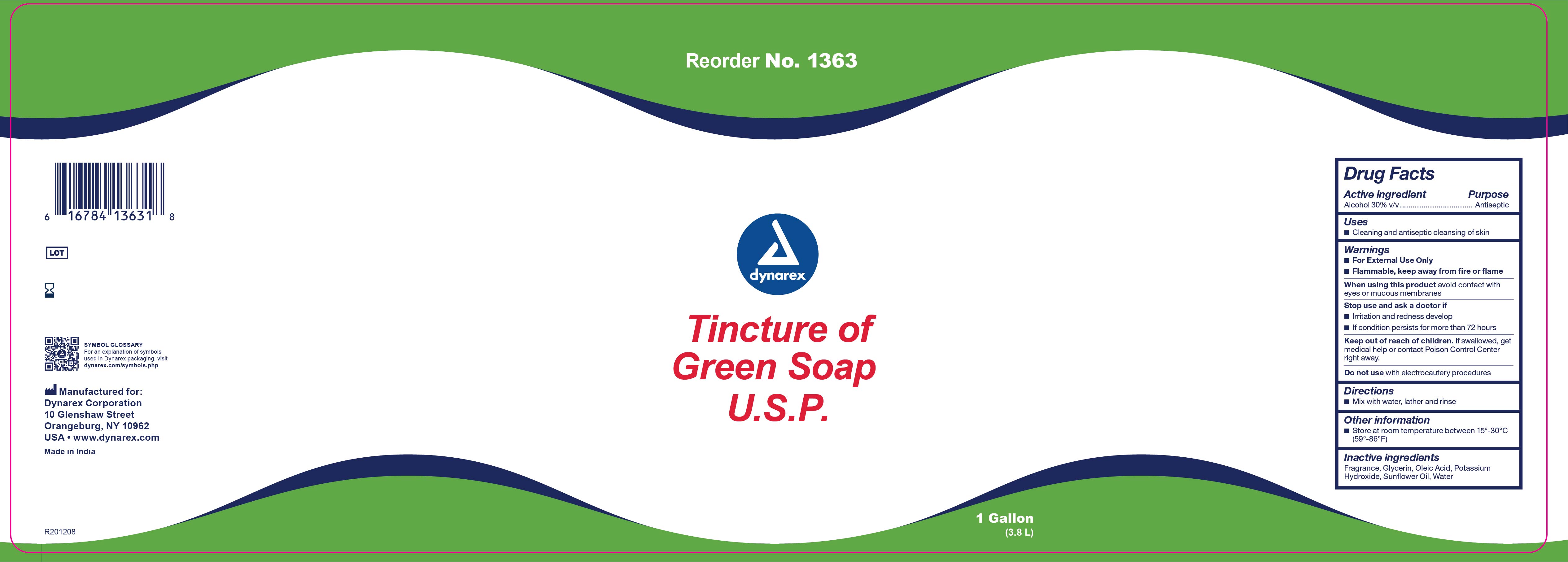 DRUG LABEL: Dynarex Green
NDC: 67777-308 | Form: LIQUID
Manufacturer: Dynarex Corporation
Category: otc | Type: HUMAN OTC DRUG LABEL
Date: 20241120

ACTIVE INGREDIENTS: ALCOHOL 0.3 mL/1 mL
INACTIVE INGREDIENTS: OLEIC ACID; POTASSIUM HYDROXIDE; WATER; GLYCERIN; SUNFLOWER OIL

1362 Dynarex Green Soap NDC 67777-308-01
1363 Dynarex Green Soap NDC 67777-308-02

ACTIVE INGREDIENT

Active Ingredient Purpose

Alcohol, 30% v/v Antiseptic

WARNINGS

- For external use only
- Flammable, keep away from fire or flame
- Avoid contact with eyes and mucousal membranes

Do not use with electrocautery procedures

PURPOSE

An antiseptic wash.

INDICATIONS & USAGE

Cleaning and antiseptic cleansing of skin.

DOSAGE & ADMINISTRATION

Mix with water, lather and rinse off.

KEEP OUT OF REACH OF CHILDREN, if swallowed get medical help or contact a Poison Control Center right away.

OTHER INFORMATION

- Store at room temperature: 15o - 30o C (59o - 86o F)
- Avoid excessive heat

INACTIVE INGREDIENTS

Inactive ingredients: Coconut acid, fragrance, glycerin, oleic acid, potassium hydroxide, water.